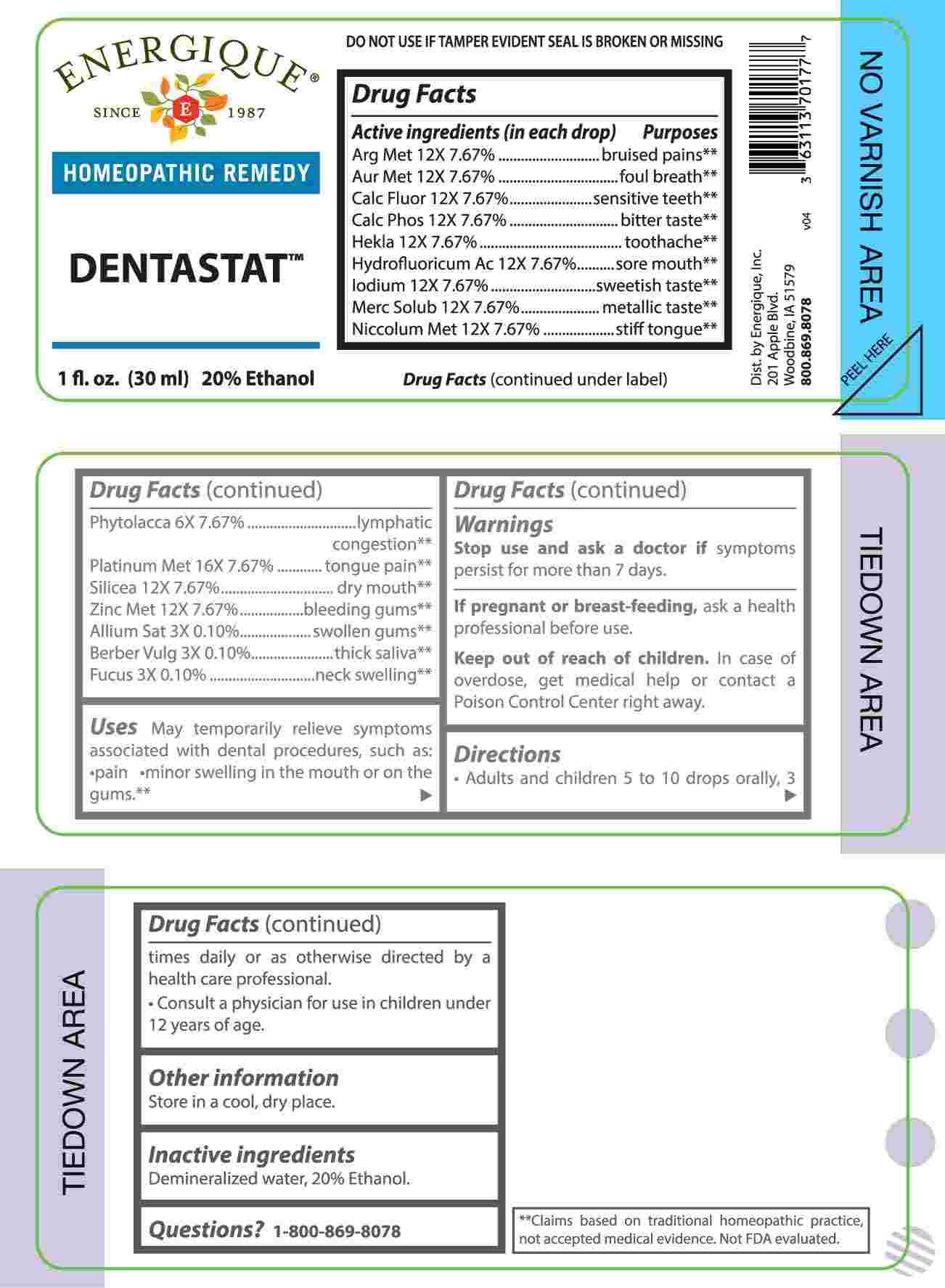 DRUG LABEL: Dentastat
NDC: 44911-0661 | Form: LIQUID
Manufacturer: Energique, Inc.
Category: homeopathic | Type: HUMAN OTC DRUG LABEL
Date: 20241024

ACTIVE INGREDIENTS: GARLIC 3 [hp_X]/1 mL; BERBERIS VULGARIS ROOT BARK 3 [hp_X]/1 mL; FUCUS VESICULOSUS 3 [hp_X]/1 mL; PHYTOLACCA AMERICANA ROOT 6 [hp_X]/1 mL; SILVER 12 [hp_X]/1 mL; GOLD 12 [hp_X]/1 mL; CALCIUM FLUORIDE 12 [hp_X]/1 mL; TRIBASIC CALCIUM PHOSPHATE 12 [hp_X]/1 mL; HEKLA LAVA 12 [hp_X]/1 mL; HYDROFLUORIC ACID 12 [hp_X]/1 mL; IODINE 12 [hp_X]/1 mL; MERCURIUS SOLUBILIS 12 [hp_X]/1 mL; NICKEL 12 [hp_X]/1 mL; SILICON DIOXIDE 12 [hp_X]/1 mL; ZINC 12 [hp_X]/1 mL; PLATINUM 16 [hp_X]/1 mL
INACTIVE INGREDIENTS: WATER; ALCOHOL

DRUG FACTS:

ACTIVE INGREDIENTS:

(in each drop) Argentum Metallicum 12X 7.67%, Aurum Metallicum 12X 7.67%, Calcarea Fluorica 12X 7.67%, Calcarea Phosphorica 12X 7.67%, Hekla Lava 12X 7.67%, Hydrofluoricum Acidum 12X 7.67%, Iodium 12X 7.67%, Mercurius Solubilis 12X 7.67%, Niccolum Metallicum 12X 7.67%, Phytolacca Decandra 6X 7.67%, Platinum Metallicum 16X 7.67%, Silicea 12X 7.67%, Zincum Metallicum 12X 7.67%, Allium Sativum 3X 0.10%, Berberis Vulgaris 3X 0.10%, Fucus Vesiculosus 3X 0.10%.

PURPOSES:

Argentum Metallicum – bruised pains**, Aurum Metallicum – foul breath**, Calcarea Fluorica – sensitive teeth**, Calcarea Phosphorica – bitter taste**, Hekla Lava – toothache**, Hydrofluoricum Acidum – sore mouth**, Iodium – sweetish taste**, Mercurius Solubilis – metallic taste**, Niccolum Metallicum – stiff tongue**, Phytolacca Decandra – lymphatic congestion**, Platinum Metallicum – tongue pain**, Silicea - dry mouth**, Zincum Metallicum – bleeding gums**, Allium Sativum – swollen gums**, Berberis Vulgaris – thick saliva**, Fucus Vesiculosus – neck swelling**.
**Claims based on traditional homeopathic practice, not accepted medical evidence. Not FDA evaluated.

USES:

May temporarily relieve symptoms associated with dental procedures, such as: pain and minor swelling in the mouth or on the gums.**

** Claims based on traditional homeopathic practice, not accepted medical evidence. Not FDA evaluated.

WARNINGS:

Stop use and ask a doctor if symptoms persist for more than 7 days.

If pregnant or breast-feeding, ask a health professional before use.

Keep out of reach of children. In case of overdose, get medical help or contact a Poison Control Center right away.

DO NOT USE IF TAMPER EVIDENT SEAL IS BROKEN OR MISSING. Store in a cool, dry place.

KEEP OUT OF REACH OF CHILDREN:

In case of overdose, get medical help or contact a Poison Control Center right away.

DIRECTIONS:

• Adults and children 5 to 10 drops orally, 3 times daily or as otherwise directed by a health care professional.

• Consult a physician for use in children under 12 years of age.

INACTIVE INGREDIENTS:

Demineralized water, 20% Ethanol.

QUESTIONS:

Dist. by Energique, Inc.

201 Apple Blvd.

Woodbine, IA 51579

800.869.8078

PACKAGE LABEL DISPLAY:

ENERGIQUE

SINCE 1987

HOMEOPATHIC REMEDY

DENTASTAT

1 fl. oz. (30 ml)